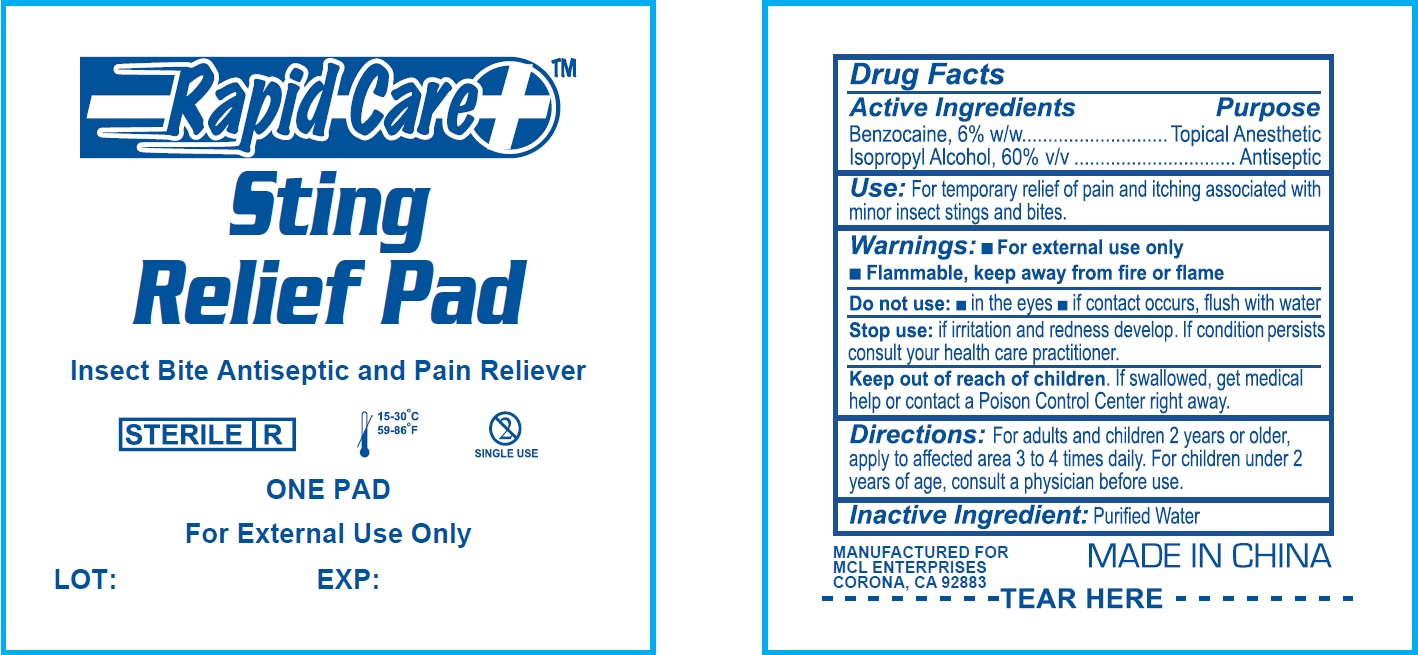 DRUG LABEL: Sting Relief
NDC: 71622-002 | Form: PATCH
Manufacturer: MCL Enterprises
Category: otc | Type: HUMAN OTC DRUG LABEL
Date: 20171228

ACTIVE INGREDIENTS: BENZOCAINE 60 mg/1 g; ISOPROPYL ALCOHOL 600 mg/1 g
INACTIVE INGREDIENTS: WATER

Sting Relief Pad

Active Ingredient

Benzocaine, 6% w/w

Isopropyl Alcohol, 60% v/v

Purpose

Topical Anesthetic

Antiseptic

Use:

For temporary relief of pain and itching associated with minor insect stings and bites.

Warnings:

- Flammable, keep away from fire or flame

Do not use:

- in the eyes
- if contact occurs, flush with water

Stop use:

- if irritation and redness develop. If condition persists consult your health care practitioner.

Keep out of reach of children.

If swallowed, get medical help or contact a Poison Control Center right away.

Directions:

For adults and children 2 years of older, apply to affected area 3 to 4 times daily. For children under 2 years of age, consult a physician before use.

Inactive Ingredient:

Purified Water